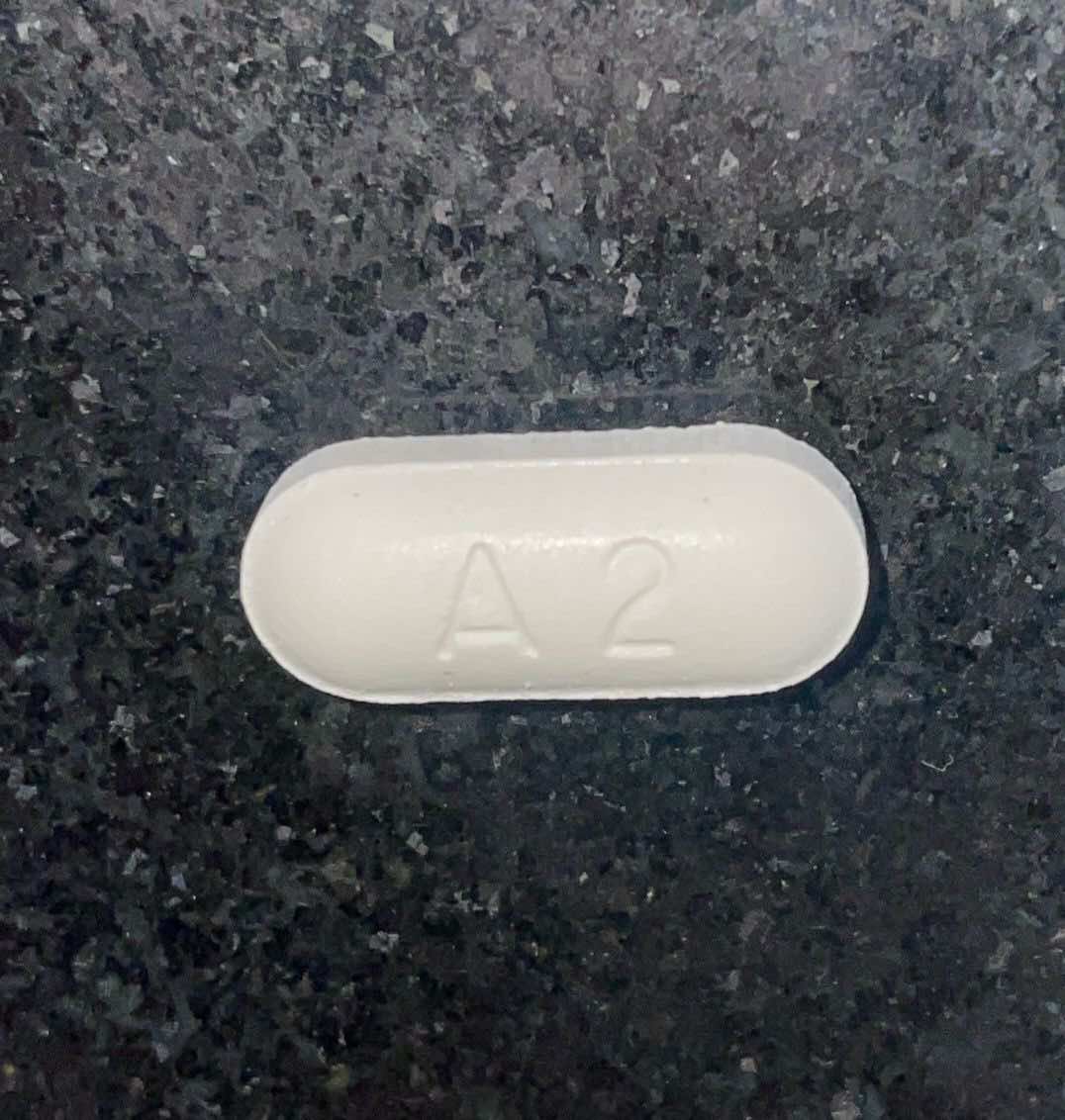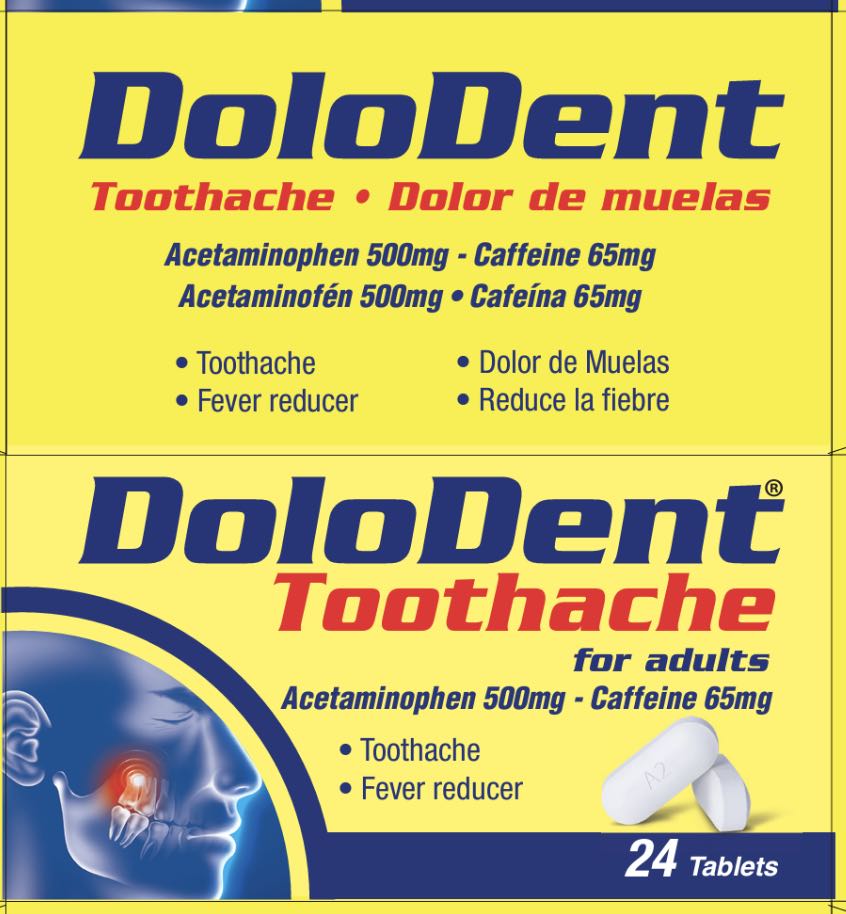 DRUG LABEL: DoloDent Toothache
NDC: 55758-435 | Form: TABLET
Manufacturer: Pharmadel LLC
Category: otc | Type: HUMAN OTC DRUG LABEL
Date: 20240919

ACTIVE INGREDIENTS: CAFFEINE 65 mg/1 1; ACETAMINOPHEN 500 mg/1 1
INACTIVE INGREDIENTS: CROSCARMELLOSE SODIUM; POVIDONE K30; MICROCRYSTALLINE CELLULOSE 101; STEARIC ACID; SILICON DIOXIDE; WATER

Dolodent Toothache (V)

Drug Facts

Active ingredients and Purposes

PURPOSE

Active ingredients | Purposes
Acetaminophen 500 mg................... | Pain reliever/fever reducer
Caffeine 65 mg................................. | Pain reliever aid

Uses

For the temporary relief of minor aches and pains due to:

- toothache
- headache
- and to reduce fever

Warnings

Liver warning: This product contains acetaminophen. Severe liver damage may occur if you take

- more than 8 tablets in 24 hours, which is the maximum daily amount for this product
- with other drugs containing acetaminophen
- 3 or more alcoholic drinks every day while using this product

Allergy alert: Acetaminophen may cause severe skin reactions. Symptoms may include:

- skin reddening
- blisters
- rash. If a skin reaction occurs, stop use and seek medical help right away.

Caffeine: The recommended dose of this product contains about as much caffeine as a cup of coffee. Limit the use of caffeine -containing medications, foods, or beverages while taking this product because too much caffeine may cause nervousness, irritability, sleeplessness, and, occasionally, rapid heartbeat.

Do not use

- with any other drug containing acetaminophen (prescription or non-prescription). If you are not sure whether a drug contains acetaminophen, ask a doctor or pharmacist.
- if allergic to any of the ingredients in this product
- on children under 12 years of age

Ask a doctor before use if you have

- liver disease

Ask a doctor before use if you are

- taking the blood thinning drug warfarin

Stop use and ask a doctor or dentist if

- pain gets worse or lasts more than 10 days
- fever gets worse or lasts more than 3 days
- redness or swelling is present
- any new symptoms appear

If pregnant or breastfeeding,

ask a health professional before use.

KEEP OUT OF REACH OF CHILDREN.

OVERDOSE WARNING: Taking more than the recommended dose (overdose) may cause liver damage. In case of overdose, get medical help or contact a Poison Control Center right away. Prompt medical attention is critical for adults as well as for children even if you do not notice any signs or symptoms.

Directions

- do not take more than directed (see OVERDOSE WARNING)
- adults and children 12 years of age and older: take 2 tablets, every 6 hours while symptoms last. Do not take more than 8 tablets in 24 hours
- children under 12 years of age: do not use

Other information

- store between 68°-77°F (20°-25°C)

Inactive ingredients

croscarmellose sodium, microcrystalline cellulose 101, povidone k30, silicon dioxide, stearic acid, water

Questions?

+1-866-359-3478 (M-F) 9 AM to 5 PM EST or www.pharmadel.com

Distributed by / Distribuido por:

PHARMADEL LLC

New Castle, DE, 19720